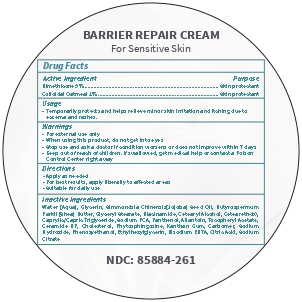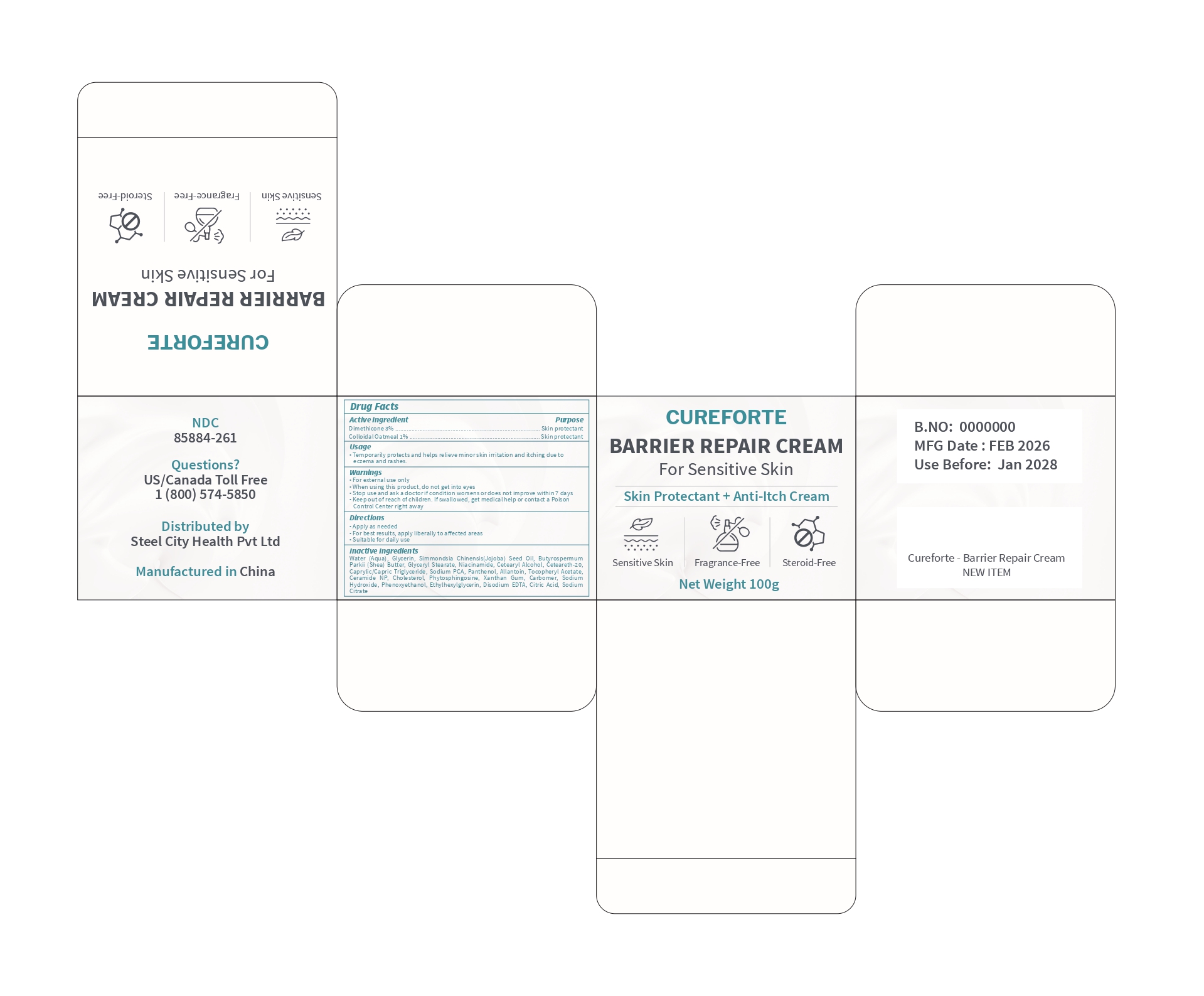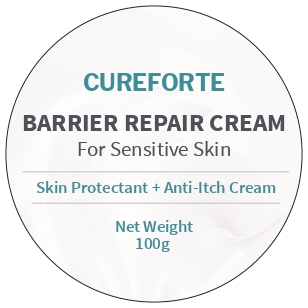 DRUG LABEL: Barrier Repair
NDC: 85884-261 | Form: CREAM
Manufacturer: Steel City Health Private Limited
Category: otc | Type: HUMAN OTC DRUG LABEL
Date: 20260131

ACTIVE INGREDIENTS: OATMEAL 0.0025 g/1 g; DIMETHICONE 350 0.03 g/1 g
INACTIVE INGREDIENTS: PHENOXYETHANOL; GLYCERYL STEARATE SE; ALLANTOIN; GLYCERIN; BUTYROSPERMUM PARKII (SHEA) BUTTER; NIACINAMIDE; ETHYLHEXYLGLYCERIN; CITRIC ACID; SODIUM HYDROXIDE; PHYTOSPHINGOSINE; SODIUM PCA; CHOLESTEROL; PANTHENOL; CETEARYL ALCOHOL; CERAMIDE NP; AQUA; CAPRYLIC/CAPRIC TRIGLYCERIDE; XANTHAN GUM; CARBOMER 940; SIMMONDSIA CHINENSIS (JOJOBA) SEED OIL; .ALPHA.-TOCOPHEROL ACETATE

BarrierProtect Soothing cream

DOSAGE AND ADMINISTRATION

as per Dr Dosage and Administration as per Diretions